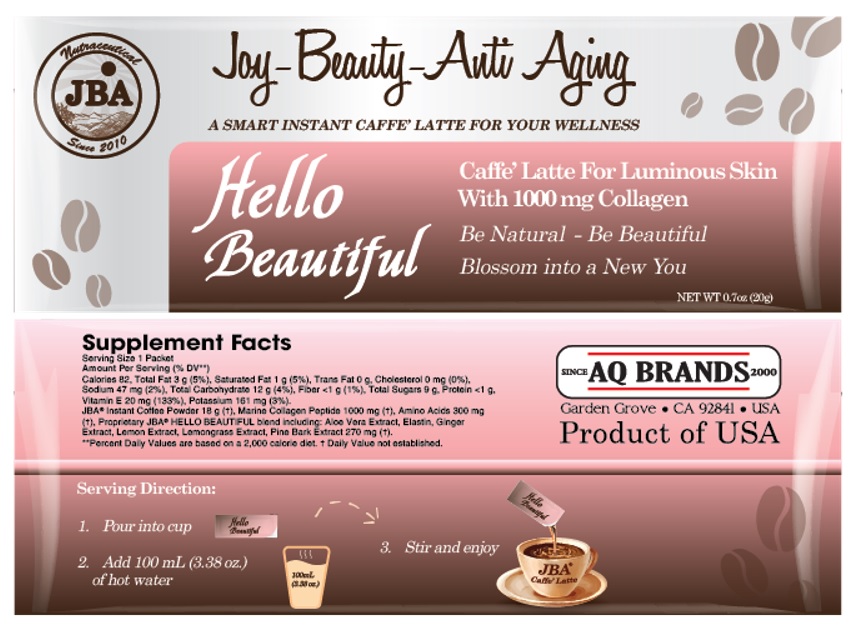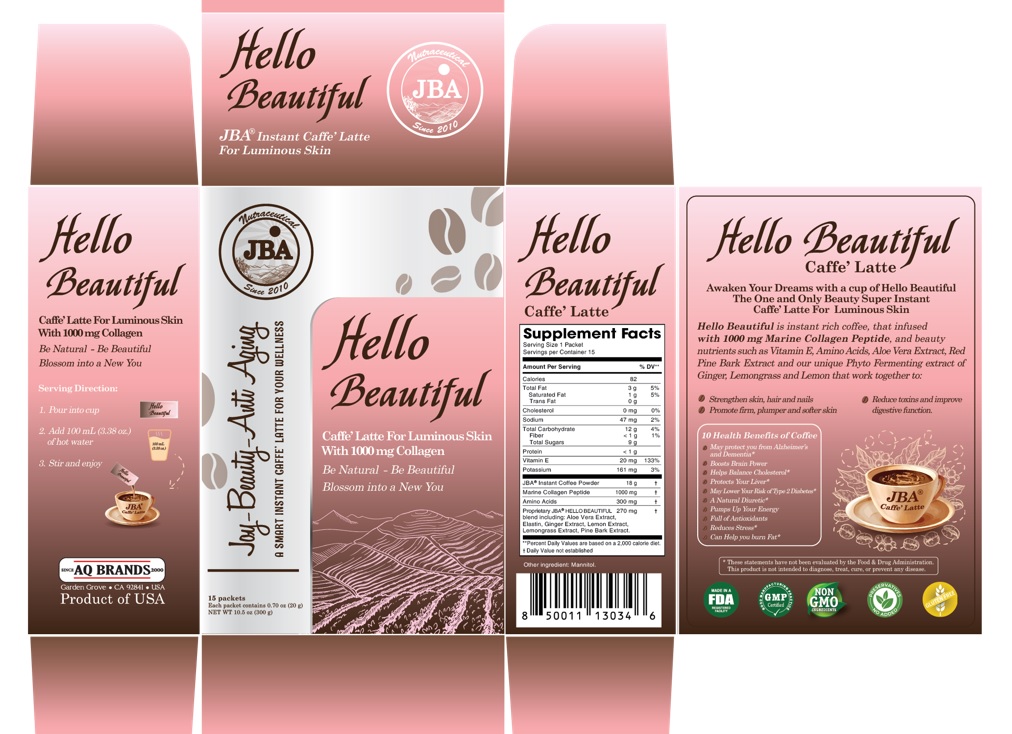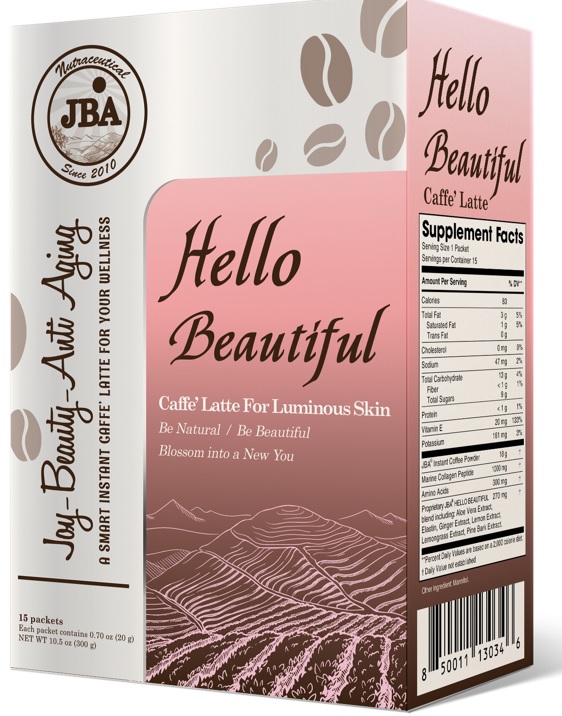 DRUG LABEL: JBA Hello Beautiful Caffe Latte
NDC: 13411-876 | Form: POWDER
Manufacturer: Advanced Pharmaceutical Services, Inc. Dba Affordable Quality Pharmaceuticals
Category: other | Type: DIETARY SUPPLEMENT
Date: 20210913

ACTIVE INGREDIENTS: .ALPHA.-TOCOPHEROL 20 mg/20 g; POTASSIUM 161 mg/20 g; COFFEE BEAN 18 g/20 g; MARINE COLLAGEN, SOLUBLE 1000 mg/20 g; AMINO ACIDS, SOURCE UNSPECIFIED 300 mg/20 g; ALOE VERA LEAF 100 mg/20 g; ELASTIN BOVINE 10 mg/20 g; GINGER 35 mg/20 g; LEMON 35 mg/20 g; CYMBOPOGON CITRATUS LEAF 30 mg/20 g; MARITIME PINE 60 mg/20 g
INACTIVE INGREDIENTS: MANNITOL

Identity

Dietary supplement

Direction

1. Pour into cup
2. Add 100 mL (3.38 oz.) of hot water
3. Stir and enjoy.

Safe handling warning

JBA® Hello Beautiful Caffe’ Latte For Luminous Skin With 1000 mg Collagen
Be Natural - Be Beautiful
Blossom into a New You
JBA® Hello Beautiful Caffe’ Latte Awaken Your Dreams with a cup of Hello Beautiful

The One and Only Beauty Super Instant Caffe’ Latte For Luminous Skin

Hello Beautiful is instant rich coffee, that infused with 1000 mg Marine Collagen Peptide , and beauty nutrients such as Vitamin E, Amino Acids, Aloe Vera Extract, Red Pine Bark Extract and our unique Phyto Fermenting extract of Ginger, Lemongrass and Lemon that work together to:
- Strengthen skin, hair and nails
- Promote firm, plumper and softer skin
Reduce toxins and improve digestive function.

10 Health Benefits of Coffee
- May protect you from Alzheimer’s and Dementia*
- Boosts Brain Power
- Helps Balance Cholesterol*
- Protects Your Liver*
- May Lower Your Risk of Type 2 Diabetes*
- A Natural Diuretic*
- Pumps Up Your Energy
- Full of Antioxidants
- Reduces Stress*
- Can Help you burn Fat*
* These statements have not been evaluated by the Food & Drug Administration. This product is not intended to diagnose, treat, cure, or prevent any disease.